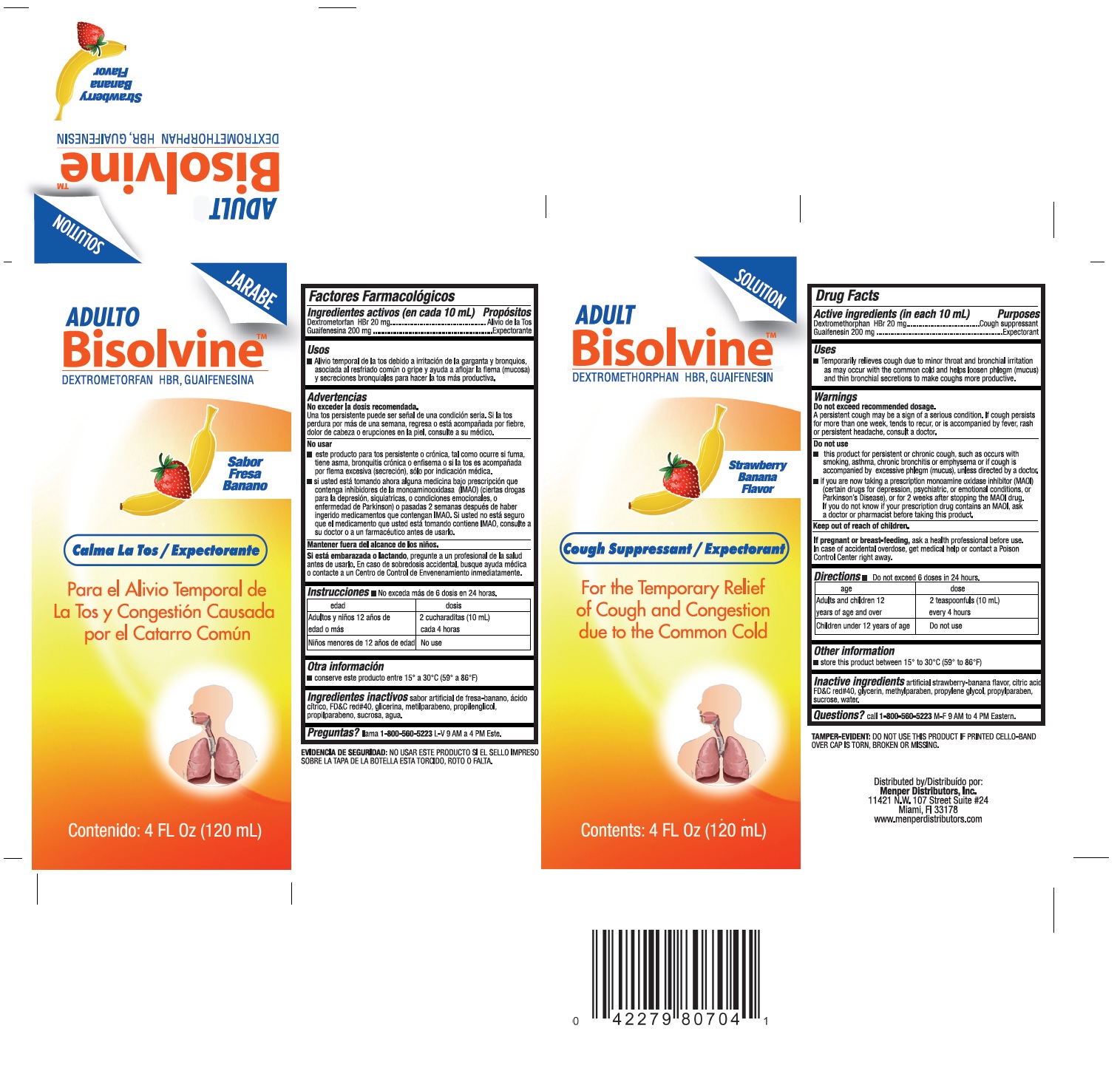 DRUG LABEL: Bisolvine
NDC: 53145-325 | Form: LIQUID
Manufacturer: MENPER DISTRIBUTORS INC.
Category: otc | Type: HUMAN OTC DRUG LABEL
Date: 20220218

ACTIVE INGREDIENTS: DEXTROMETHORPHAN HYDROBROMIDE 20 mg/10 mL; GUAIFENESIN 200 mg/10 mL
INACTIVE INGREDIENTS: CITRIC ACID MONOHYDRATE; FD&C RED NO. 40; METHYLPARABEN; GLYCERIN; PROPYLENE GLYCOL; PROPYLPARABEN; WATER; SUCROSE

Active Ingredients (in each 10 mL) Purpose

Dextromethorphan 20 mg.............................................. Cough Suppressant

Guaifenesin 200 mg ...................................................... Expectorant

Purpose

Cough Suppressant

Expectorant

Uses

temporarily relieves cough due to minor throat and bronchial irritation as may occur with the common cold and helps loosen phlegm (mucus) and thin bronchial secretions to make coughs more productive.

Warnings

Do not exceed recommended dosage.
A persistent or chronic cough may be a sign of a serious condition. If cough persists for more than one week, tends to recur, or is accompanied by fever, rash, or persistent headache, consult a doctor.

Do not use:

- this product for persistent or chronic cough, such as occurs with smoking, asthma, chronic brochitis or emphysema or if cough is accompanied by excessive phlegm (mucus), unless directed by a doctor.

* If you are now taking a prescription monoamine oxidase inhibitor (MAOI) (certain drugs for depression, psychiatric, or emotional conditions, or Parkinson's Disease), or for 2 weeks after stopping the MAOI drug. If you do not know if your prescription drug contains an MAOI, ask a doctor or pharmacist before taking this product.

Keep out of reach of children

PREGNANCY OR BREAST FEEDING

If pregnant or breast-feeding, ask a health professional before use. In case of accidental overdose, get medical help or contact a Poison Control Center right away.

Directions

Do not exceed 6 doses in 24 hours

Age | Dose
Adults and Children 12 years of age and over | 2 teaspoonfuls (10 ml) every 4 hours
Children under 12 years of age | Do not use

Inactive ingredients

artificial strawberry-banana flavor, citric acid, fd&c red #40, glycerin, methyl paraben, propylene glycol, propylparaben, sucrose, water

Questions?

Questions? call 1-800-560-5523 M-F 9 AM to 4 PM Eastern.